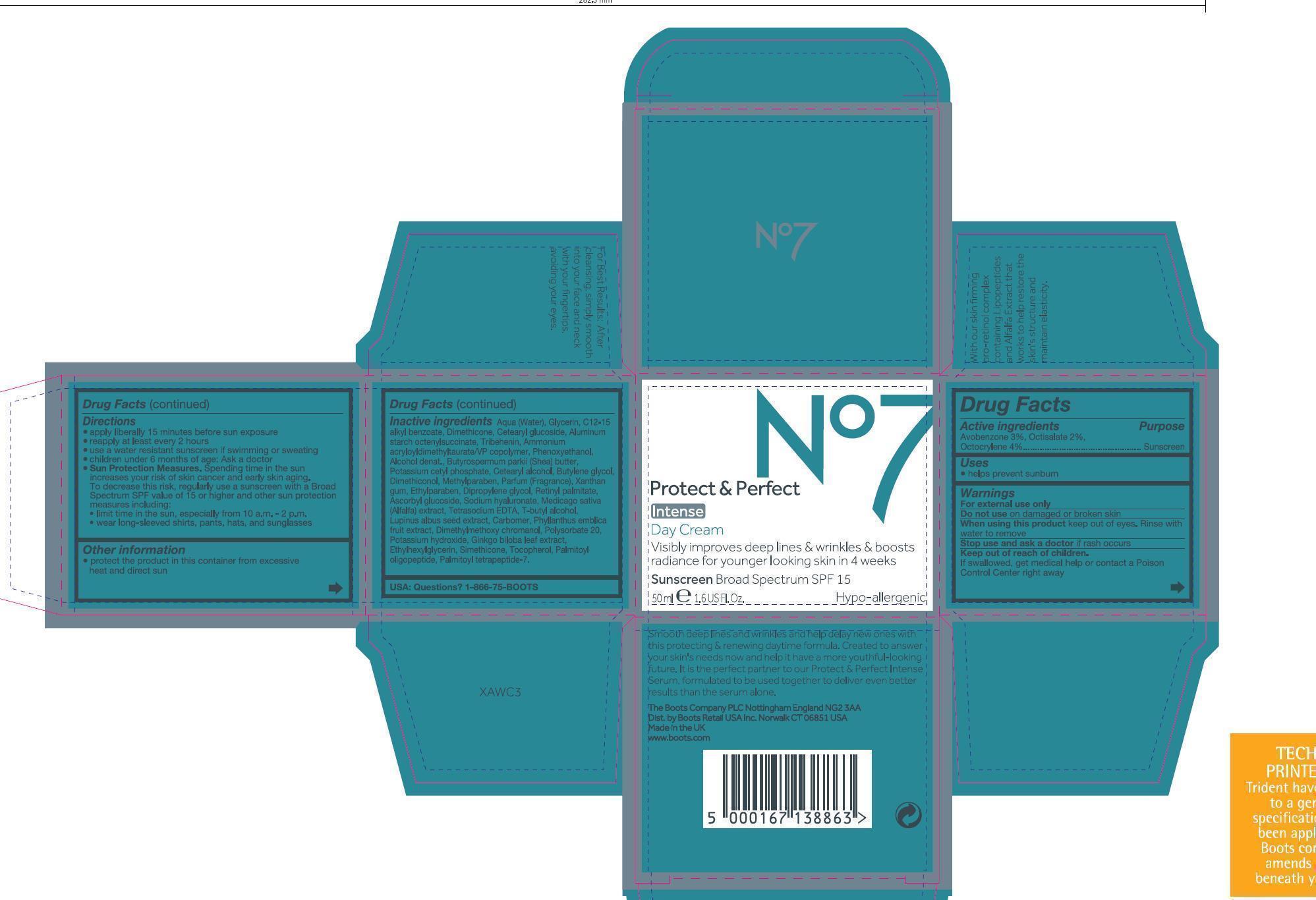 DRUG LABEL: No7 Protect and Perfect Intense Day Cream Sunscreen Broad Spectrum SPF 15
NDC: 11489-077 | Form: CREAM
Manufacturer: BCM Ltd
Category: otc | Type: HUMAN OTC DRUG LABEL
Date: 20121218

ACTIVE INGREDIENTS: Avobenzone 1.5 g/50 g; Octocrylene 2 g/50 g; Octisalate 1 g/50 g
INACTIVE INGREDIENTS: Water; Glycerin; ALKYL (C12-15) BENZOATE; Dimethicone; CETEARYL GLUCOSIDE; ALUMINUM STARCH OCTENYLSUCCINATE; Tribehenin; AMMONIUM ACRYLOYLDIMETHYLTAURATE/VP COPOLYMER; Phenoxyethanol; Alcohol; SHEA BUTTER; POTASSIUM CETYL PHOSPHATE; CETOSTEARYL ALCOHOL; Butylene glycol; methylparaben; Xanthan gum; ETHYLPARABEN; DIPROPYLENE GLYCOL; VITAMIN A PALMITATE; ASCORBYL GLUCOSIDE; HYALURONATE SODIUM; ALFALFA; EDETATE SODIUM; TERT-BUTYL ALCOHOL; LUPINUS ALBUS SEED; PHYLLANTHUS EMBLICA FRUIT; polysorbate 20; potassium hydroxide; ginkgo; ethylhexylglycerin; tocopherol; PALMITOYL OLIGOPEPTIDE; PALMITOYL TETRAPEPTIDE-7

No7 Protect and Perfect Intense Day Cream

ACTIVE INGREDIENT

Active Ingredients Avobenzone 3.0%, Octisalate 2%, Octocrylene 4%

Purpose Sunscreen

PURPOSE

Uses helps prevent sunburn

Warnings

For external use only

Do not use on damaged or broken skin

When using this product keep out if eyes. Rinse with water to remove.

Stop use and ask a doctor if rash occurs.

Keep out of reach of children. If swallowed get medical help or contact a poison control center right away.

INDICATIONS AND USAGE

Directons

Apply liberally 15 minutes before sun exposure

Use a water resistant sunscreen if swimming or sweating

Reapply at least every 2 hours

Chidren under 6 months of age: Ask a doctor

Sun Protection Measures

Spending time in the sun increases your risk of skin cancer and early skin aging. To decrease this risk, regularly use a sunscreen with a broad spectrum SPF value of 15 or higher and other sun protection measures including:

limit time in the sun, especially from 10a,m - 2p.m

wear long-sleeved shirts, pants, hats, and sunglasses

Other information

Protect the product in this container from excessive heat and direct sun

Inactive Ingredients

Aqua (water), Glycerin, C12-15 alkyl benzoate, Dimethicone, Cetearryl glucoside, Aluminum starch octenylsuccinate, Tribehenin, Ammonium acryloyldimethyltaurate/VP copolymer, phenoxyethanol, Alcohol denta.,Butyrospermum parkii (shea) butter, Potassium cetyl phosphate, Cetearyl alcohol, Butylene glycol, Dimethiconol, Methylparaben, Parfum (fragrance), Xanthan gum, Ethylparaben, Dipropylene glycol, Retinyl palmitate, Ascorby glucoside, Sodium hyaluronate, Medicago sativa (alfalfa) extract, Tetrasodium EDTA, T-butyl alcohol, Lupinus albus seed extract, Carbomer, Phyllanthus emblica fruit extract, Dimethylmethoxy chromanol, Polysorbate 20, Potassium hydroxide, Ginkgo biloba leaf extract, Ethylhexylglycerin, Simethicone, Tocopherol, Palmitoyl oligopeptide, Palmitoyl tetrapeptide-7

USA: Questions? 1-866-75-BOOTS

DESCRIPTION

Smooth deep lines and wrinkles and help delay new ones with this protecting and renewing daytime formula. Created to answer your skin's needs now and help it have a more youthful-looking future. It is the perfect partner to our Protect and Perfect Intense Serum, formulated to be used together to deliver even better results than the serum alone.

PATIENT COUNSELING INFORMATION

The Boots Company PLC Nottingham England NG2 3AA
Dist. by Boots Retail USA Inc. Norwalk CT 06851 USA
Made in the UK
www.Boots.com

DESCRIPTION

For best results: After cleansing, simply smooth into your face and neck with your fingertips, avoiding your eyes.

With our skin firming pro-retinol complex containing Lipopeptides and Alfalfa extract that works to help restore the skin's structure and maintain elasticity.

Jar

Active ingredients: Avobenzone 3%, Octisalate 2.%, Octocrylene 4%

warning

JAR TEXT

Warning: Avoid contact with eyes. If product gets into the eyes rinse well with water immediately.

DESCRIPTION

JAR TEXT

Smooth into your face and neck after applying your No7 serum.

PATIENT COUNSELING INFORMATION

JAR TEXT

The Boots Company PLC

Nottingham England NG2 3AA
Dist. by Boots Retail USA Inc.

Norwalk CT 06851 USA
Made in the UK
www.Boots.com